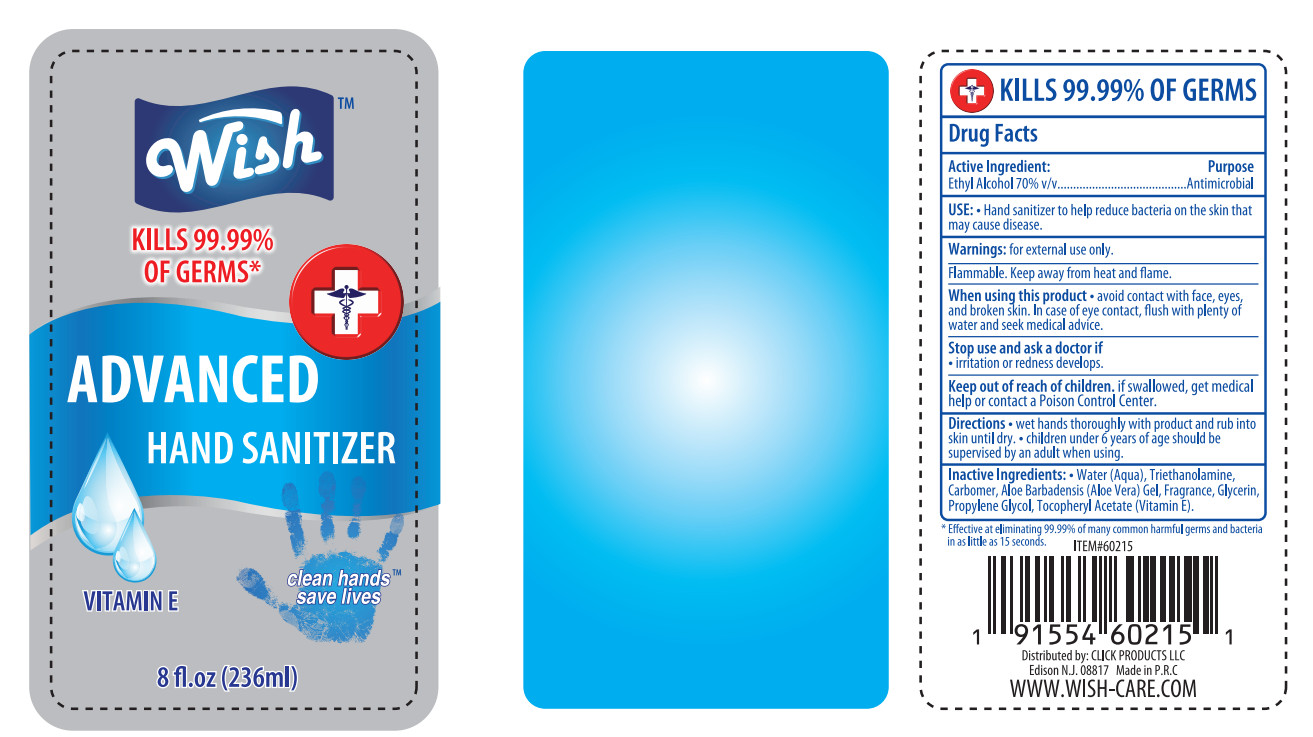 DRUG LABEL: Wish Advanced Hand Sanitizer
NDC: 71611-021 | Form: SOLUTION
Manufacturer: Click Products LLC
Category: otc | Type: HUMAN OTC DRUG LABEL
Date: 20220104

ACTIVE INGREDIENTS: ALCOHOL 70 mL/100 mL
INACTIVE INGREDIENTS: GLYCERIN; PROPYLENE GLYCOL; WATER; CARBOMER 934; TROLAMINE; ALPHA-TOCOPHEROL ACETATE; ALOE VERA WHOLE

NA

Active Ingredient(s)

Ethyl Alcohol 70% v/v

Purpose

Antimicrobial

Use

Hand sanitizer to help reduce bacteria on the skin that may cause disease

Warnings

For external use only

Flammable. Keep away from heat and flame

When using this product aviod contact with face, eyes and broken skin. In case of contact, flush with plenty of water and seek medical advice

Stop use and ask a doctor if irritation or redness develops

Keep out of reach of children. If swallowed, get medical help or contact a Poison Control Center right away.

Directions

- Wet hands thoroughly with product and rub into skin until dry
- Children under 6 years of age should be supervised by an adult when using

Inactive ingredients

Water, triethanolamine, carbomer, aloe barbadensis (aloe vera) gel, fragrance, propylene glycol, glycerin, tocopheryl acetate (Vitamin E)